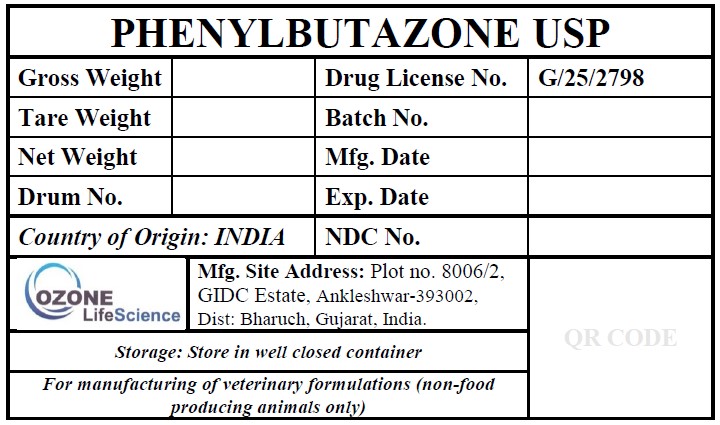 DRUG LABEL: PHENYLBUTAZONE
NDC: 87453-001 | Form: POWDER
Manufacturer: OZONE LIFE SCIENCE
Category: other | Type: BULK INGREDIENT - ANIMAL DRUG
Date: 20260223

ACTIVE INGREDIENTS: PHENYLBUTAZONE 1 kg/1 kg

PHENYLBUTAZONE USP